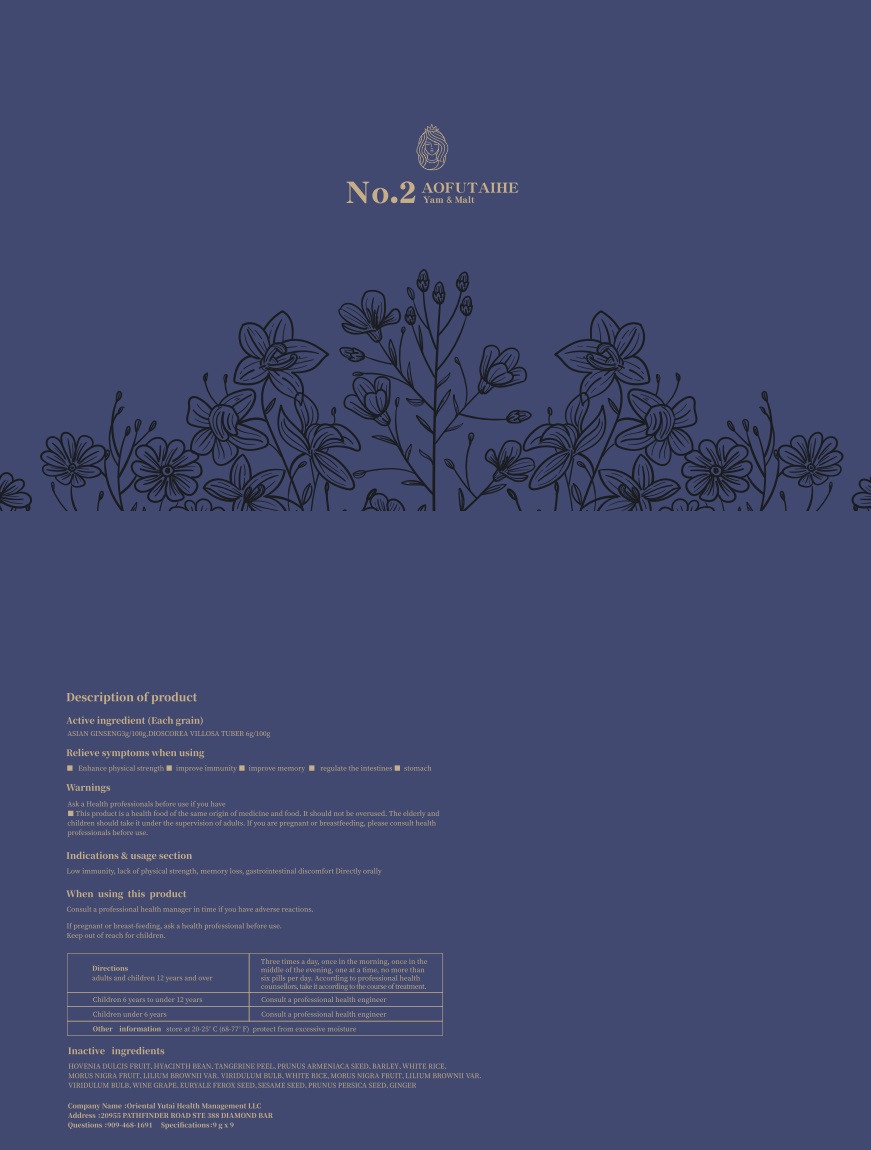 DRUG LABEL: DIOSCOREA VILLOSA CAKE
NDC: 83494-004 | Form: OINTMENT, AUGMENTED
Manufacturer: Oriental Yutai Health Management LLC
Category: homeopathic | Type: HUMAN OTC DRUG LABEL
Date: 20230602

ACTIVE INGREDIENTS: DIOSCOREA VILLOSA TUBER 6 g/100 g; ASIAN GINSENG 3 g/100 g
INACTIVE INGREDIENTS: TANGERINE PEEL; PRUNUS ARMENIACA SEED; WHITE RICE; HOVENIA DULCIS FRUIT; MORUS NIGRA FRUIT; SESAME SEED; LILIUM BROWNII VAR. VIRIDULUM BULB; PRUNUS PERSICA SEED; HYACINTH BEAN; BARLEY; WINE GRAPE; EURYALE FEROX SEED; GINGER

Active ingredients

ASIAN GINSENG 3% w/w

DIOSCOREA VILLOSA TUBER 6% w/w

Relieve symptoms when using

■ Enhance physical strength ■ improve immunity

■ improve memory ■ regulate the intestines ■ stomach

Indications & usage section

Low immunity, lack of physical strength, memory loss, gastrointestinal discomfort Directly orally

Warnings

Ask a Health professionals before use if you have

■This product is a health food of the same origin of medicine and food. It should not be overused. The elderly and children should take it under the supervision of adults. If you are pregnant or breastfeeding, please consult health professionals before use.

Keep out of reach for children.

When using this product

Consult a professional health manager in time if you have adverse reactions.
If pregnant or breast-feeding, ask a health professional before use.

Directions

adults and children 12 years and over

three times a day, once in the morning, once in the middle of the evening, one at a time, no more than six pills per day. According to professional health counsellors, take it according to the course of treatment.

children 6 years to under 12 years

Consult a professional health engineer

children under 6 years

Consult a professional health engineer

Inactive ingredients

HOVENIA DULCIS FRUIT、HYACINTH BEAN、TANGERINE PEEL、PRUNUS ARMENIACA SEED、BARLEY、WHITE RICE、MORUS NIGRA FRUIT、LILIUM BROWNII VAR. VIRIDULUM BULB、WINE GRAPE、EURYALE FEROX SEED、SESAME SEED、PRUNUS PERSICA SEED、GINGER